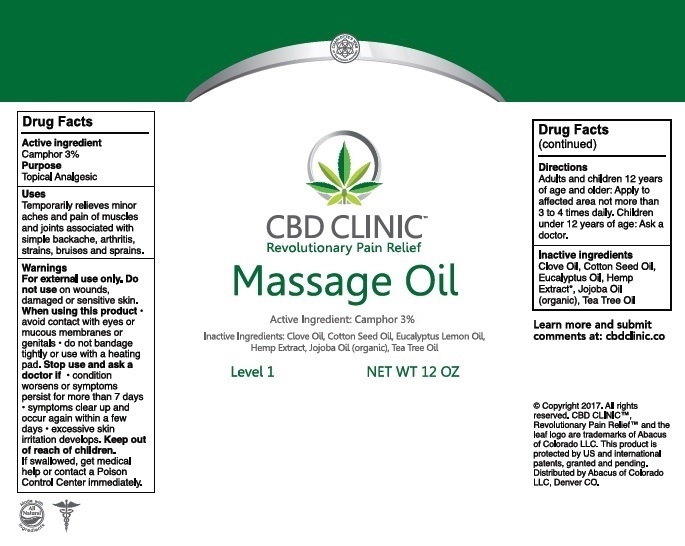 DRUG LABEL: CBD Clinic - Massage Oil - Level 1
NDC: 24909-711 | Form: OIL
Manufacturer: Aidance Skincare & Topical Solutions, LLC
Category: otc | Type: HUMAN OTC DRUG LABEL
Date: 20170515

ACTIVE INGREDIENTS: CAMPHOR (SYNTHETIC) 0.03 kg/1 kg
INACTIVE INGREDIENTS: CLOVE OIL; COTTONSEED OIL; EUCALYPTUS OIL; HEMP; JOJOBA OIL; TEA TREE OIL

Drug Facts

Active Ingredients

Camphor 3%

Purpose

Camphor - Topical Analgesic

Uses

Temporarily relieves minor aches and pains of muscles and joints associated with simple backache, arthritis, strains, bruises and sprains.

Warnings

For external use only. Do not use on wounds or damaged skin. When using this product - avoid contact with eyes or mucous membranes - do not bandage tightly or use with heating pad. Stop use and ask a doctor if - condition worsens or symptoms persist for more than 7 days - symptoms clear up and occur again within a few days - excessive skin irritation develops.

Keep out of reach of children.

If swallowed, get medical help or contact a Poison Control Center immediately.

Directions

Adults and children 12 years of age and older: Apply to affected area not more than 3 to 4 times daily. Children under 12 years of age: Ask a doctor.

Inactive Ingredients

Clove Oil, Cotton Seed Oil, Eucalyptus Oil, Hemp Extract, Jojoba Oil (organic), Tea Tree Oil

PRINCIPAL DISPLAY PANEL - 12 Oz. Size

CBD CLINIC
Revolutionary Pain Relief
Massage Oil
Active Ingredient: Camphor 3%
Inactive Ingredients: Clove Oil, Cotton Seed Oil, Eucalyptus Lemon Oil, Hemp Extract, Jojoba Oil (organic), Tea Tree Oil
Level 1 NET WT 12 OZ